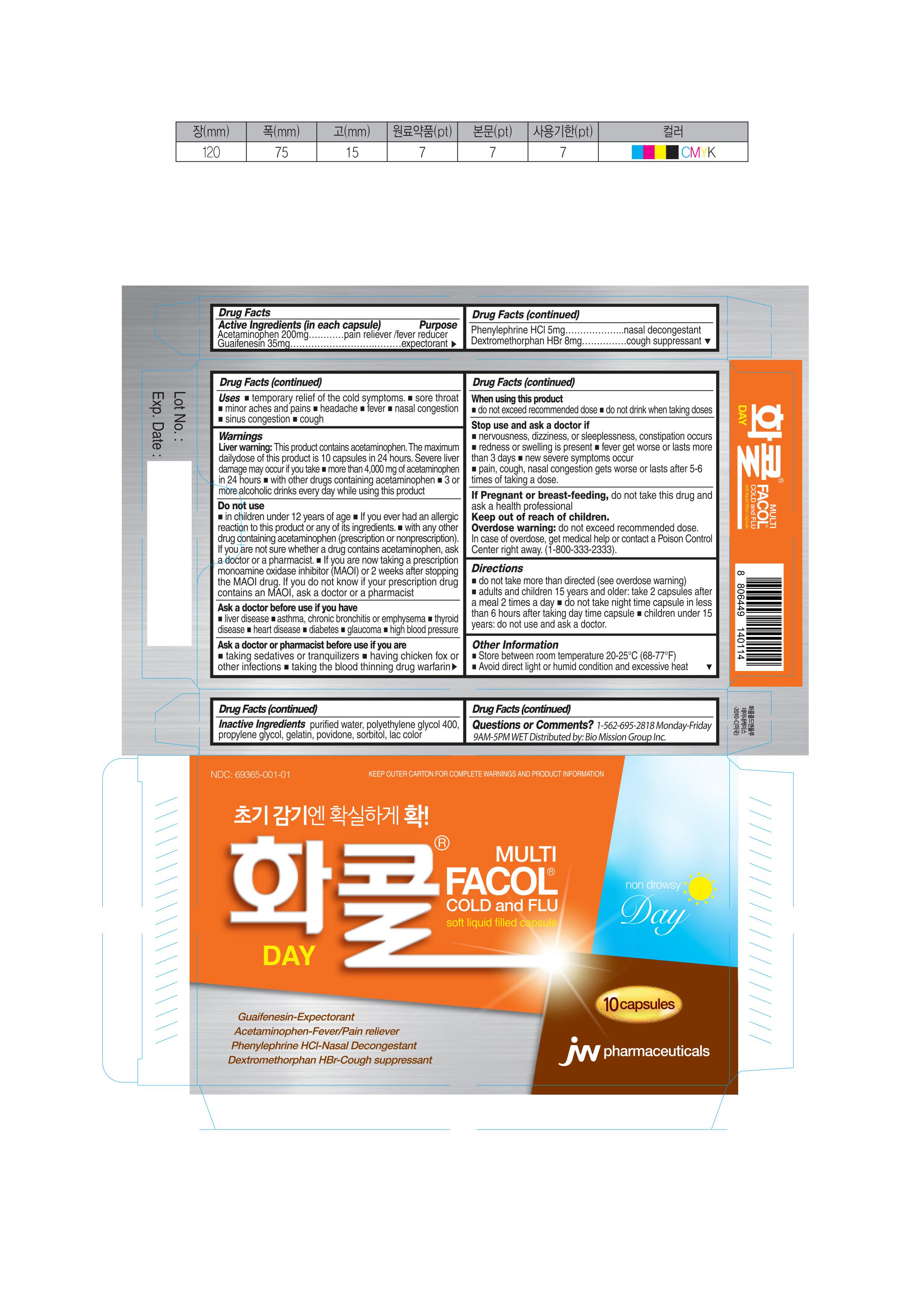 DRUG LABEL: Facol Cold and Flu Day
NDC: 69365-001 | Form: CAPSULE, LIQUID FILLED
Manufacturer: JW Holdings
Category: otc | Type: HUMAN OTC DRUG LABEL
Date: 20240828

ACTIVE INGREDIENTS: ACETAMINOPHEN 200 mg/1 1; GUAIFENESIN 35 mg/1 1; DEXTROMETHORPHAN HYDROBROMIDE 8 mg/1 1; PHENYLEPHRINE HYDROCHLORIDE 5 mg/1 1
INACTIVE INGREDIENTS: WATER 40 mg/1 1; POLYETHYLENE GLYCOL 400 459 mg/1 1; PROPYLENE GLYCOL 40 mg/1 1; GELATIN 203.93 mg/1 1; POVIDONE K29/32 33 mg/1 1; SORBITOL 141.1 mg/1 1; COCHINEAL 2.185 mg/1 1; ALUMINUM OXIDE 2.185 mg/1 1

FACOL COLD AND FLU DAY

Active Ingredient(in each tablet) Purpose

Acetaminophen 200mg ………………………………………………………….………………pain reliever /fever reducer
Guaifenesin 35mg…………………………………………………………………………….……...expectorant

Phenylephrine HCl 5mg……………………….……………………………………………....….nasal decongestant
Dextromethorphan HBr 8mg…………………………………………………cough suppression

Inactive Ingredients

purified water, polyethylene glycol 400, propylene glycol, povidone, gelatin, sorbitol, purified water, lac color

Uses

■ temporary relief of the following cold symptoms.
■ sore throat ■ minor aches and pains ■ headache ■ fever
■ nasal congestion ■ sinus congestion and pressure ■ cough

Warnings

Liver warning:

This product contains acetaminophen. The maximum daily dose of this product is 10 caplets in 24 hours.

Severe liver damage may occur if you take

■ more than 4,000 mg of acetaminophen in 24 hours
■ with other drugs containing acetaminophen

■ 3 or more alcoholic drinks every day while using this product

INDICATIONS & USAGE

Relief mild to moderately severe pain, Temporarily reduce multi cold symptom

Directions

■ Do not take more than directed (see overdose warning)
■ adults and children 15 years and older: take 2 capsules after a meal 2 times a day
■ swallow whole-do not crush, chew or dissolve
■ do not take night time capsule in less than 6 hours after taking day time capsule
■ children under 15 years: do not use and ask a doctor.

Ask a doctor before use if you have

■ liver disease
■ asthma, chronic bronchitis or emphysema
■ thyroid disease
■ heart disease

■ diabetes

■ glaucoma

■ high blood pressure

Ask a doctor or pharmacist before use if you are

■ taking sedatives or tranquilizers ■ having chicken fox or other infections
■ taking the blood thinning drug warfarin

Do not use

■ For children who are younger than 3 months old. (new born baby)
■ If you ever had an allergic reaction to this product or any of its ingredients.
■ with any other drug containing acetaminophen (prescription or nonprescription). If you are not sure whether a drug contains acetaminophen, ask a doctor or a pharmacist.
■ If you are now taking a prescription monoamine oxidase inhibitor (MAOI) (certain drugs for depression, psychiatric or emotional conditions, or Parkinson’s disease) or 2 weeks after stopping the MAOI drug. If you do not know if your prescription drug contains an MAOI, ask a doctor or a pharmacist)

If Pregnant or breast-feeding

do not take this drug and ask a health professional

Questions or Comments?

1-562-695-2818 Monday-Friday 9AM-5PM WET

Distributed by: Bio Mission Group Inc.

Stop use and ask a doctor if

■ nervousness, dizziness, or sleeplessness, constipation occurs
■ redness or swelling is present ■ fever get worse or lasts more than 3 days
■ new severe symptoms occur such as shock (anaphylaxis), Stevens Johnson Syndrome, Lyell Syndrome, Asthma, Dyshepatia or Interstitial lung diseases.
■ pain, cough, nasal congestion gets worse or lasts after 5-6 times of taking a dose.

When using this product

■ Do not exceed recommended dose
■ Do not drink when taking doses

Other Information

■ Store between room temperature 20-25°C (68-77°F)
■ Avoid direct light or humid condition and excessive heat

Overdose warning:

Do not exceed recommended dose. In case of overdose, get medical help or contact a Poison Control Center right away. (1-800-333-2333).

PRINCILA DISPLAY PANEL

NDC 69365-001-01

KEEP OUTER CARTON FOR COMPLETE WARNINGS AND PRODUCT INFORMATION

Facol® Cold and Flu Day

MULTI

Soft liquid-filled capsule

Guaifenesin-Expectorant

Acetaminophen-Fever/Pain Reducer

Phenylephrine HCl-Nasal Decongestant

Dextromethorphan HBr-Cough Suppressant

10 capsules

JW pharmaceuticals